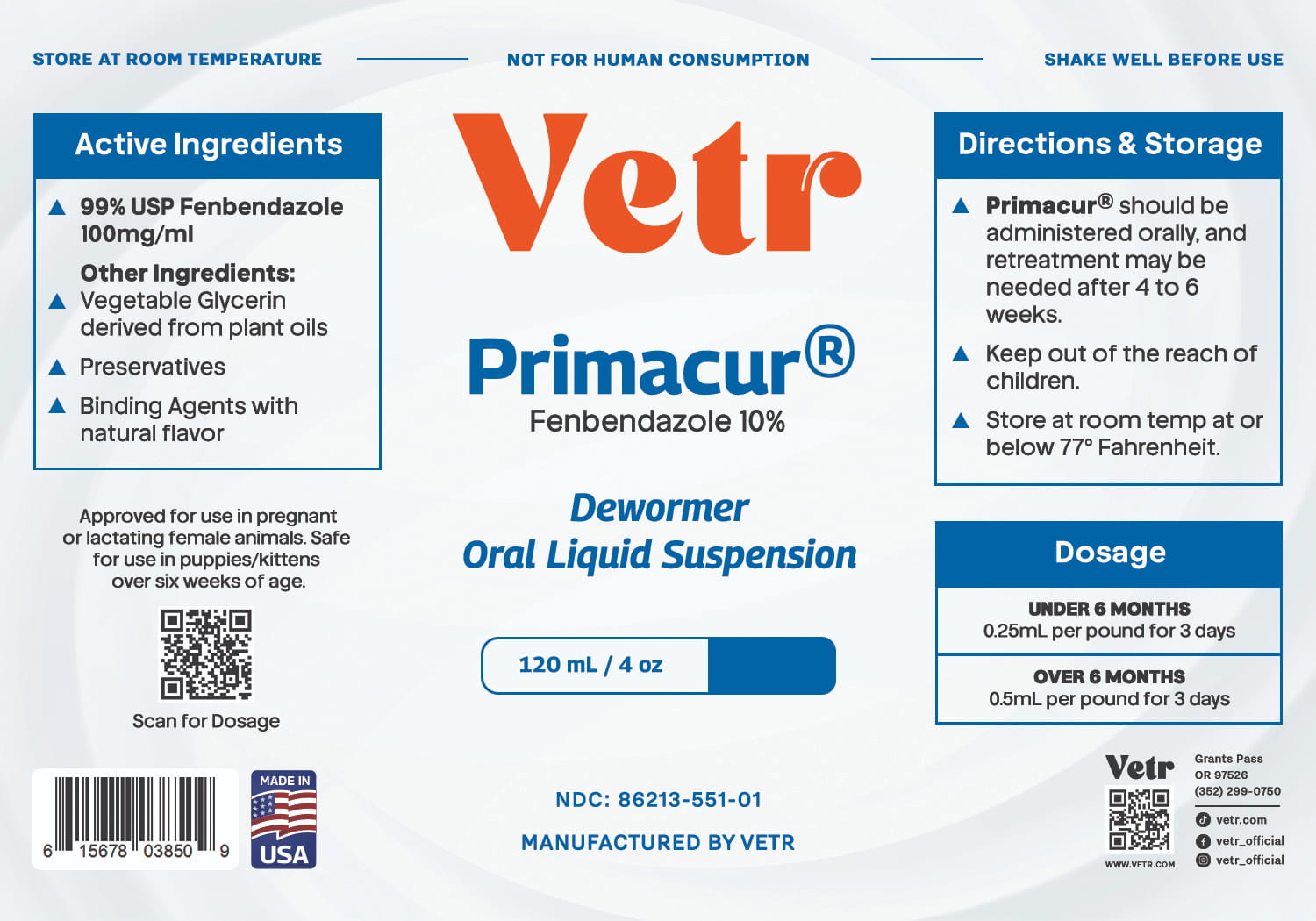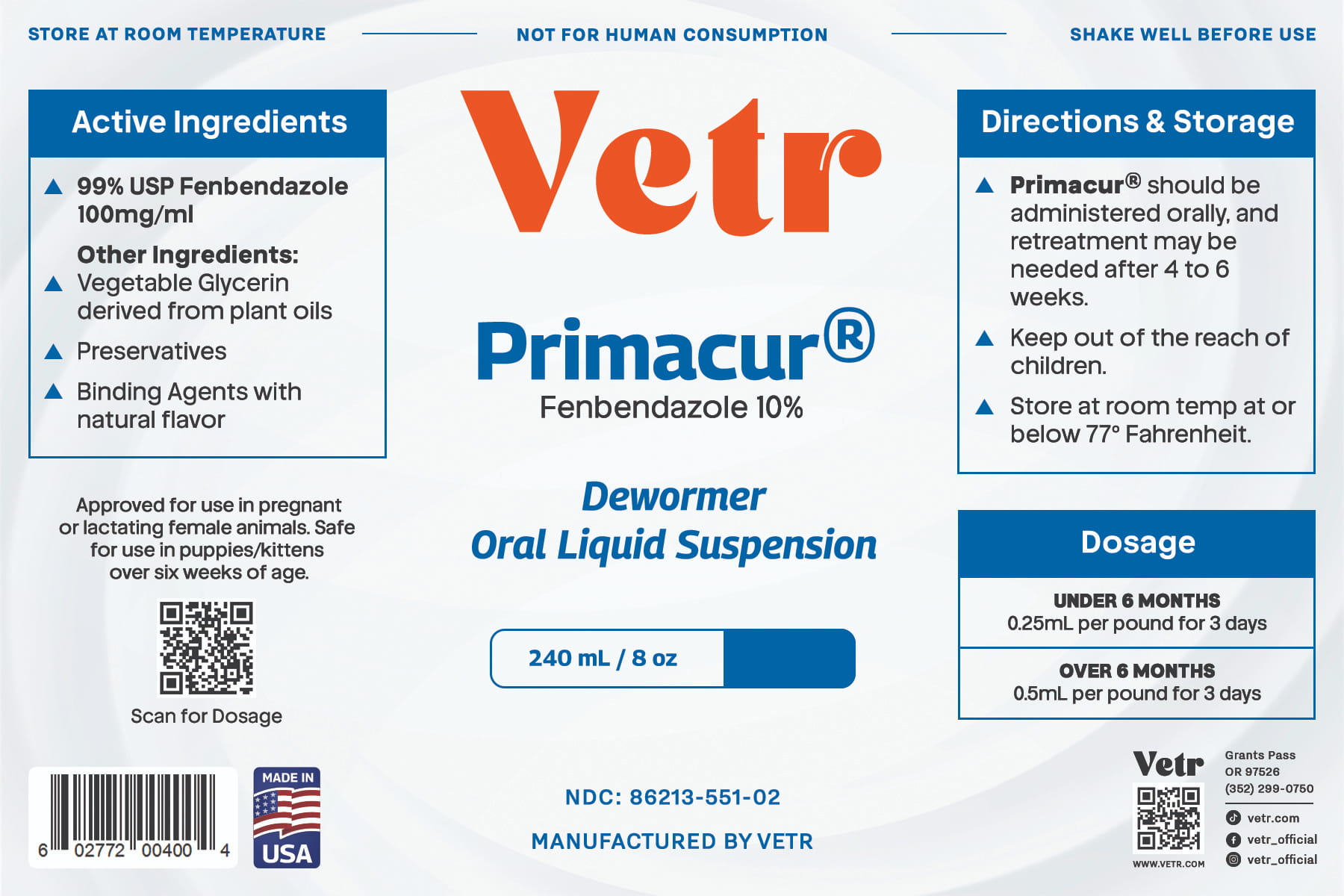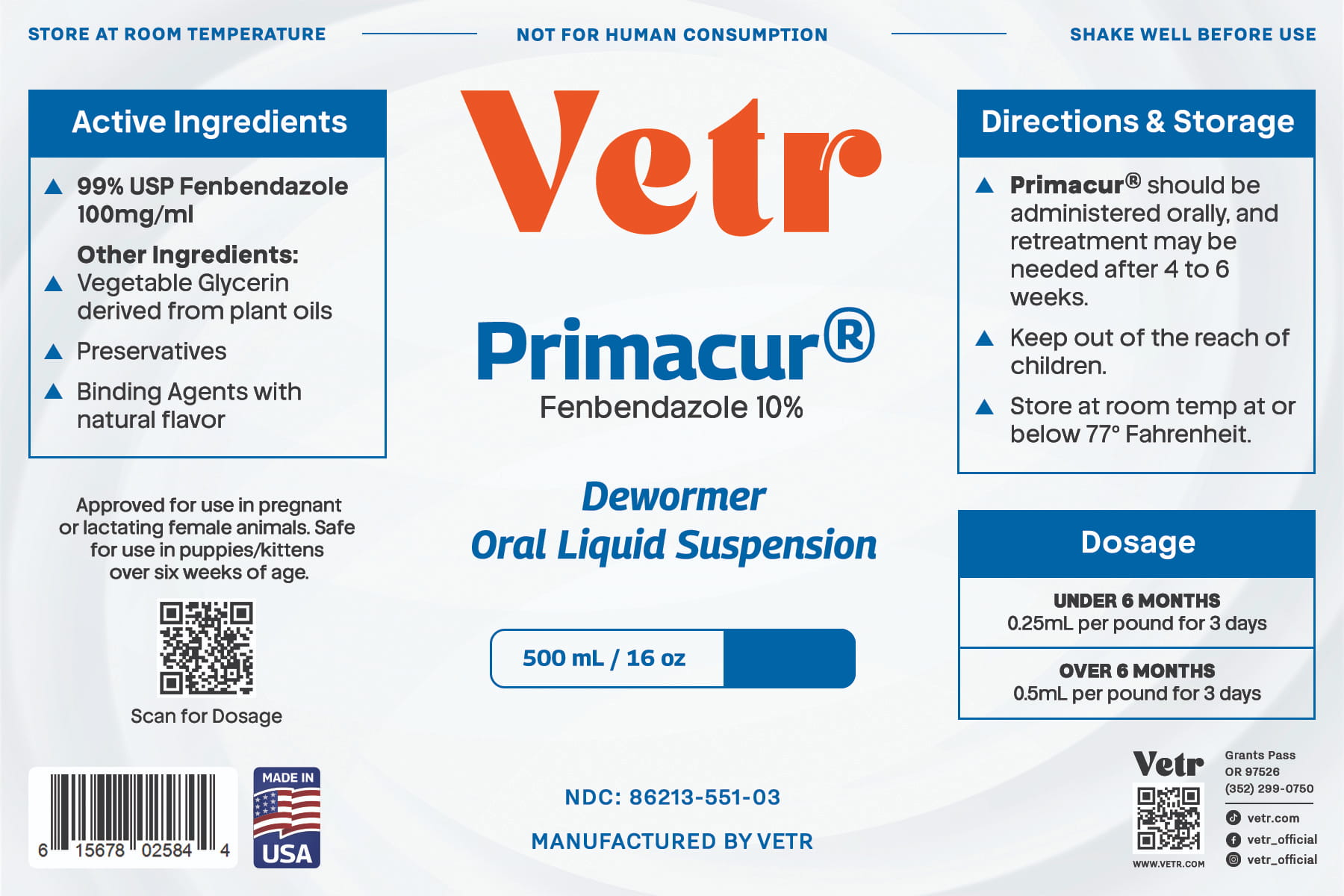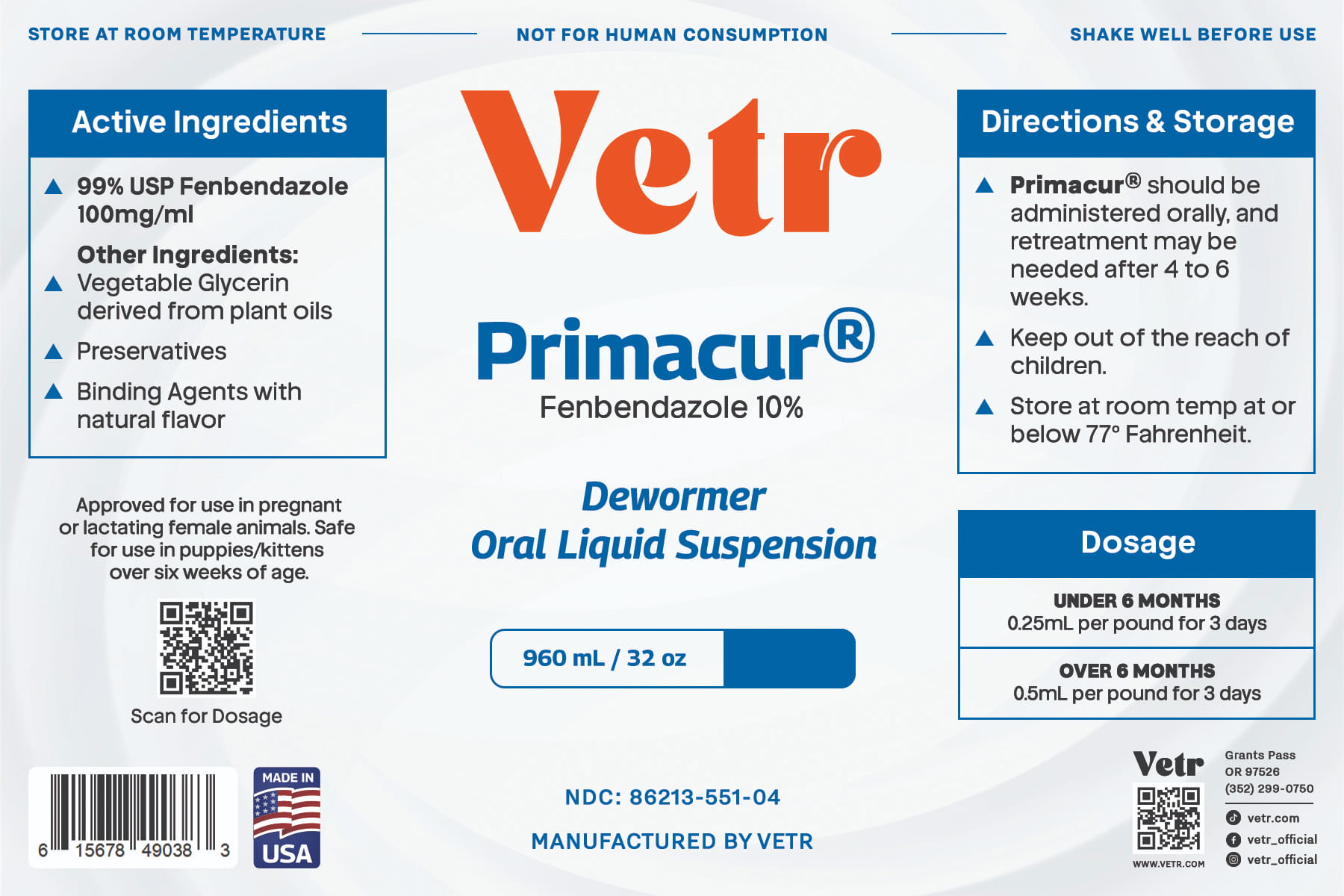 DRUG LABEL: Primacur
NDC: 86213-551 | Form: SUSPENSION
Manufacturer: Vetr LLC
Category: animal | Type: OTC ANIMAL DRUG LABEL
Date: 20260225

ACTIVE INGREDIENTS: FENBENDAZOLE 100 mg/1 mL
INACTIVE INGREDIENTS: GLYCERIN; METHYLPARABEN; PROPYLPARABEN

Vetr Primacur (10% fenbendazole oral suspension)

Caution

Shake well before use. Do not give to puppies or kittens under 6 weeks of age. May be administered to pregnant or lactating females.

Active Ingredients

fenbendazole USP, 100 mg/mL (10% w/v)

Other Ingredients

Certified vegetable glycerin, natural preservatives and binding agents

Storage

Store at room temperature at or below 25 C (<77 F)

Directions

Adminster orally once per day for 3 consecutive days. May repeat treatment after 4-6 weeks duration. For animals under 6 months of age, administer 0.25 mL per pound of body weight. For animals over 6 months of age, administer 0.5 mL per pound of body weight.

Dosage Chart (under 6 months age):

1 lb body weight 0.25 mL

5 lb body weight 1.25 mL

10 lb body weight 2.5 mL

25 lb body weight 6.25 mL

Dosage Chart (over 6 months age):

5 lb body weight 2.5 mL

10 lb body weight 5 mL

20 lb body weight 10 mL

40 lb body weight 20 mL

50 lb body weight 25 mL

Say goodbye to worms. Made in the USA. Available in 120mL, 240mL, 500 mL, 960mL and 1/2 Gal (1893mL) sizes.